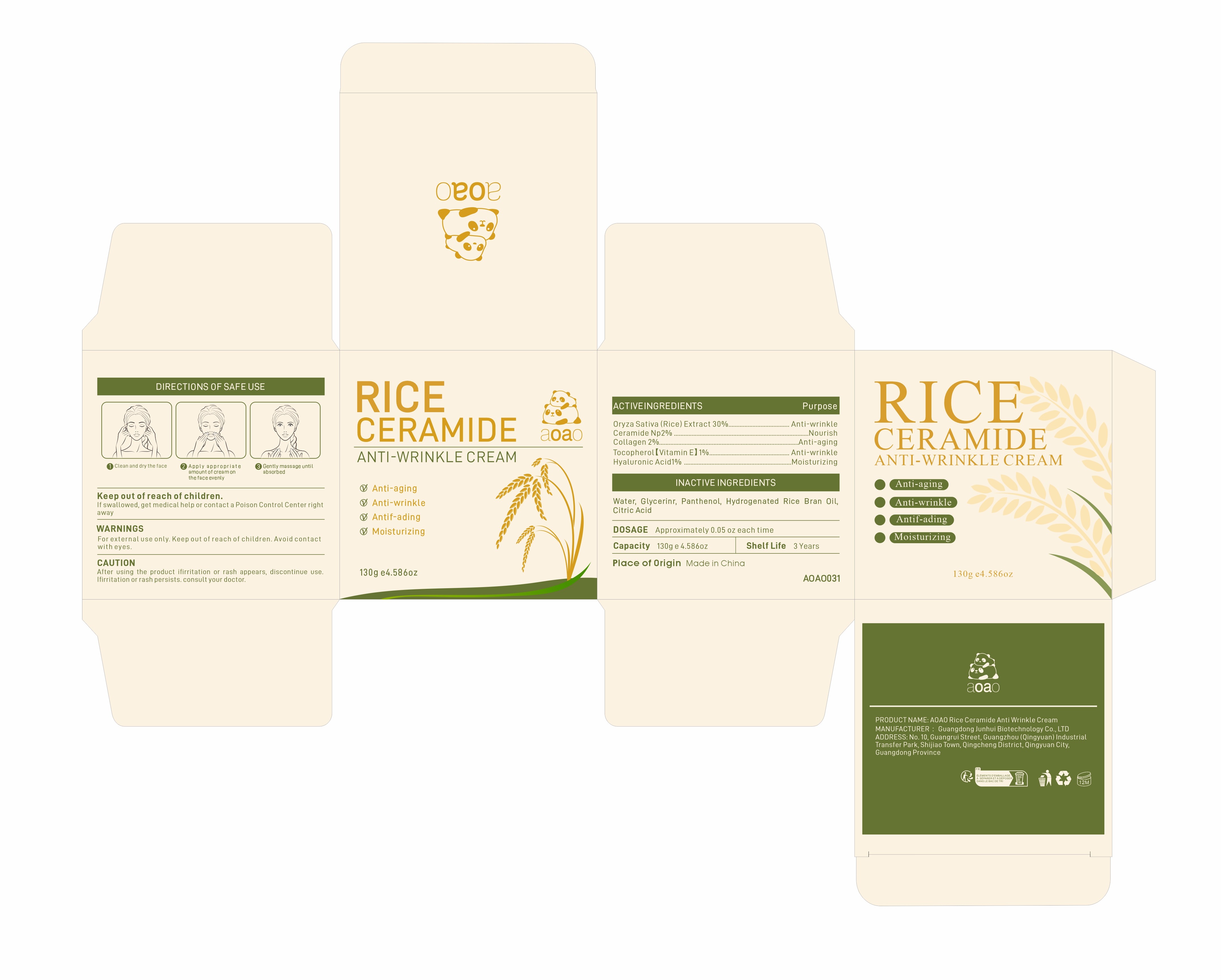 DRUG LABEL: AOAO Rice Ceramide Anti Wrinkle Cream
NDC: 84509-014 | Form: CREAM
Manufacturer: Guangdong Junhui Biotechnology Co., LTD
Category: otc | Type: HUMAN OTC DRUG LABEL
Date: 20240912

ACTIVE INGREDIENTS: RICE GERM 39000 mg/130 g; CERAMIDE AP 2600 mg/130 g; COLLAGEN, SOLUBLE, FISH SKIN 2600 mg/130 g; TOCOPHEROL 1300 mg/130 g; HYALURONIC ACID 1300 mg/130 g
INACTIVE INGREDIENTS: RICE BRAN OIL; GLYCERIN; ANHYDROUS CITRIC ACID; WATER; PANTHENOL

Active Ingredients

Oryza Sativa (Rice) Extract 30%
Ceramide NP 2%
Collagen 2%
Tocopherol【Vitamin E】 1%
Hyaluronic Acid 1%

Purpose

Anti-wrinkle
Nourish
Anti-aging
Moisturizing

Uses

1 clean and dry the face
2 Apply appropriate amount of cream on the face evenly
3 Gently massage until absorbed

Keep out of reach of children

If swallowed, get medical help or contact a Poison Control Center right away

Warnings

For external use only. Keep out ofreach of children.Avoid contact with eyes

CAUTION

After using the product ifirritation or rash appears,discontinue use.Ifirritation or
rash persists.consult your doctor.

Product Name

AOAO Rice Ceramide Anti Wrinkle Cream

D0SAGE

Approximately 0.05 oz each time

Inactive Ingredients

Water,Glycerin，Panthenol,Hydrogenated Rice Bran Oil，Citric Acid

MANUFACTURER

Guangdong Junhui Biotechnology Co., LTD

ADDRESS

No. 10, Guangrui Street, Guangzhou (Qingyuan) Industrial Transfer Park, Shijiao Town, Qingcheng District, Qingyuan City, Guangdong Province

Capacity

130g e4.586 oz

Shelf Life

3Years

Place of Origin

Made in China